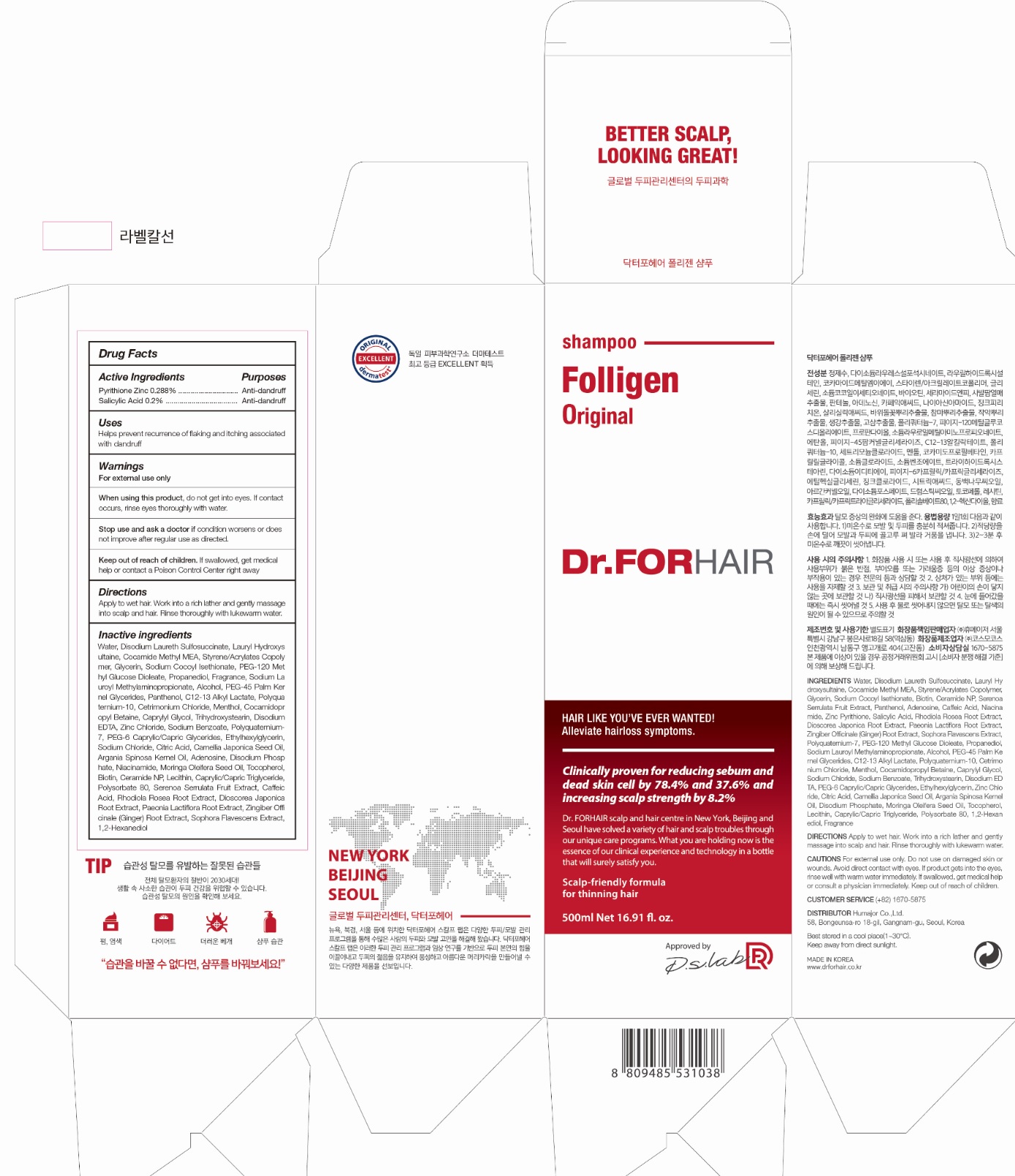 DRUG LABEL: Dr.FORHAIR FOLLIGEN
NDC: 69244-0007 | Form: SHAMPOO
Manufacturer: Humajor Co., Ltd.
Category: otc | Type: HUMAN OTC DRUG LABEL
Date: 20190807

ACTIVE INGREDIENTS: PYRITHIONE ZINC 2.88 g/100 mL; SALICYLIC ACID 2 g/100 mL
INACTIVE INGREDIENTS: WATER; DISODIUM LAURETH SULFOSUCCINATE; LAURYL HYDROXYSULTAINE; COCOYL METHYL MONOETHANOLAMINE; STYRENE/ACRYLAMIDE COPOLYMER (500000 MW); GLYCERIN; SODIUM COCOYL ISETHIONATE; PEG-120 METHYL GLUCOSE DIOLEATE; PROPANEDIOL; SODIUM LAUROYL METHYLAMINOPROPIONATE; ALCOHOL; PEG-45 PALM KERNEL GLYCERIDES; PANTHENOL; C12-13 ALKYL LACTATE; CETRIMONIUM CHLORIDE; POLYQUATERNIUM-10 (1000 MPA.S AT 2%); MENTHOL, UNSPECIFIED FORM; COCAMIDOPROPYL BETAINE; CAPRYLYL GLYCOL; TRIHYDROXYSTEARIN; EDETATE DISODIUM ANHYDROUS; ZINC CHLORIDE; SODIUM BENZOATE; POLYQUATERNIUM-7 (70/30 ACRYLAMIDE/DADMAC; 1600000 MW); ETHYLHEXYLGLYCERIN; SODIUM CHLORIDE

69244-0007_Dr.FORHAIR FOLLIGEN

ACTIVE INGREDIENT

zinc pyrithione 0.288%

Salicylic Acid 0.2%

INACTIVE INGREDIENT

Water, Disodium Laureth Sulfosuccinate, Lauryl hydroxy sultaine, Cocamide Methyl MEA, Styrene/Acrylates Copolymer, Glycerin, Sodium Cocoyl Isethionate, PEG-120 Methyl Glucose Dioleate, Propanediol, Fragrance, Sodium Lauroyl Methylaminopropionate, Alcohol, PEG-45 Palm Kernel Glycerides, Panthenol, C12-13 Alkyl Lactate, Polyquaternium-10, Cetrimonium Chloride, Menthol, Cocamidopropyl Betaine, Caprylyl Glycol, Trihydroxystearin, Disodium EDTA, Zinc Chloride, Sodium benzoate, Polyquaternium-7, PEG-6 Caprylic/Capric Glyceride , Ethylhexylglycerin, Sodium Chloride, Citric Acid, Camellia Japonica Seed Oil, Argania Spinosa Kernel Oil, Adenosine, Disodium Phosphate , Niacinamide, Moringa Oleifera Seed Oil, Tocopherol, Biotin, Ceramide NP, Lecithin, Caprylic/Capric Triglyceride, Polysorbate 80, Serenoa Serrulata Fruit Extract, Caffeic Acid, Rhodiola Rosea Root Extract, Dioscorea Japonica Root Extract, Paeonia Lactiflora Root Extract, Zingiber Officinale (Ginger) Root Extract, Sophora Flavescens Extract, 1,2-Hexanediol

PURPOSE

Antidandruff

keep out or reach of the children

INDICATIONS AND USAGE

Helps prevent recurrence of flaking and itching associated with dandruff

WARNINGS

For external use only.

When using this product, do not get into eyes. If contact occurs, rinse eyes thoroughly with water.

Stop use and ask a doctor if condition worsens or does not improve after regular use as directed.

DOSAGE AND ADMINISTRATION

Apply to wet hair. Work into a rich lather and gently massage into scalp and hair. Rinse thoroughly with lukewarm water.